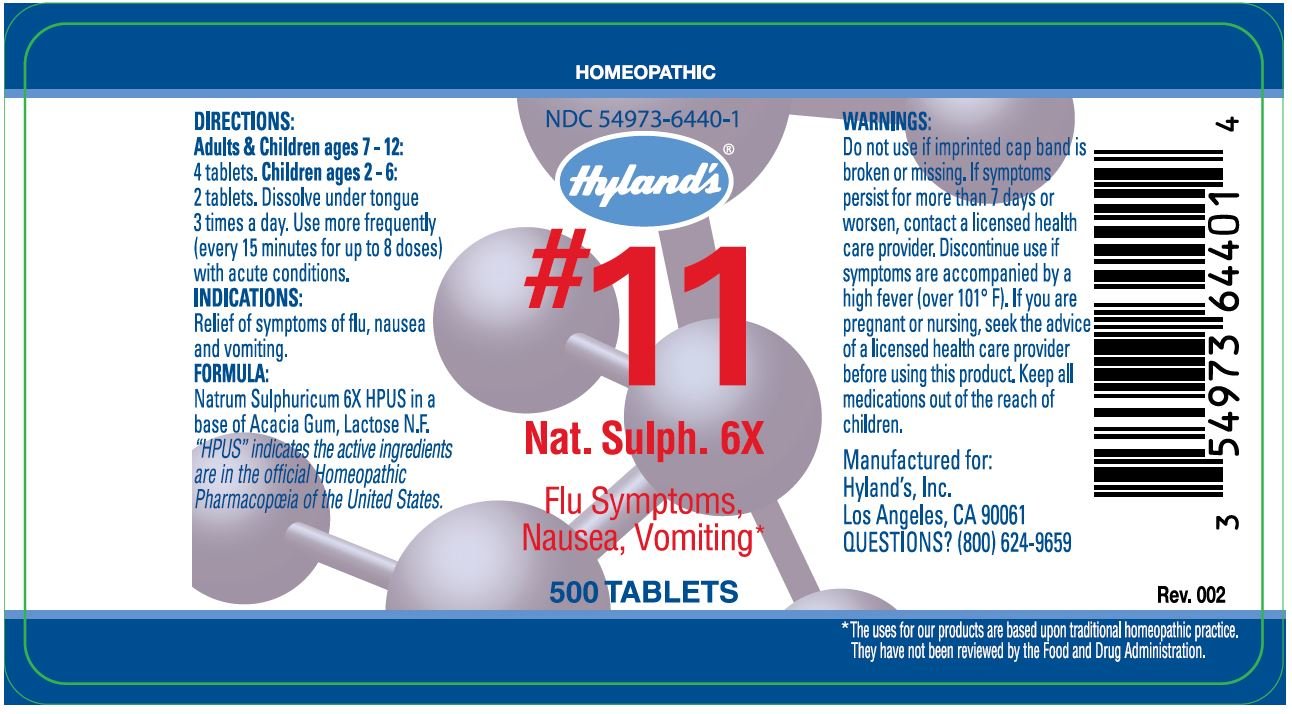 DRUG LABEL: NAT SULPH
NDC: 54973-6440 | Form: TABLET
Manufacturer: Hyland's Inc.
Category: homeopathic | Type: HUMAN OTC DRUG LABEL
Date: 20221219

ACTIVE INGREDIENTS: SODIUM SULFATE ANHYDROUS 6 [hp_X]/1 1
INACTIVE INGREDIENTS: ACACIA; LACTOSE

NAT. SULPH.

DIRECTIONS

Adults & Children ages 7 - 12: 4 tablets. Children ages 2 - 6: 2 tablets. Dissolve under tongue 3 times a day. Use more frequently (every 15 minutes for up to 8 doses) with acute conditions.

INDICATIONS

PURPOSE

Relief of symptoms of the flu,nausea and vomiting.

FORMULA

Natrum Sulphuricum 6X HPUS

INACTIVE INGREDIENT

in a base of Acacia Gum, Lactose N.F.

“HPUS” indicates that the active ingredients are in the official Homeopathic Pharmacopœia of the United States.

Warnings

Do not use if imprinted cap band is broken or missing.

ASK DOCTOR

If symptoms persist for more than 7 days or worsen, contact a licensed health care provider.

STOP USE

Discontinue use if symptoms are accompanied by a high fever (over 101° F).

PREGNANCY OR BREAST FEEDING

If you are pregnant or nursing, seek the advice of a licensed health care provider before using this product.

KEEP OUT OF REACH OF CHILDREN

Keep all medications out of the reach of children

QUESTIONS?

(800) 624-9659

PRINCIPAL DISPLAY PANEL - 500 Tablet Bottle Label

HOMEOPATHIC

NDC 54973-6440-1

Hyland's®

#11
Nat. Sulph. 6X

Flu Symptoms,

Nausea,Vomiting*

500 TABLETS